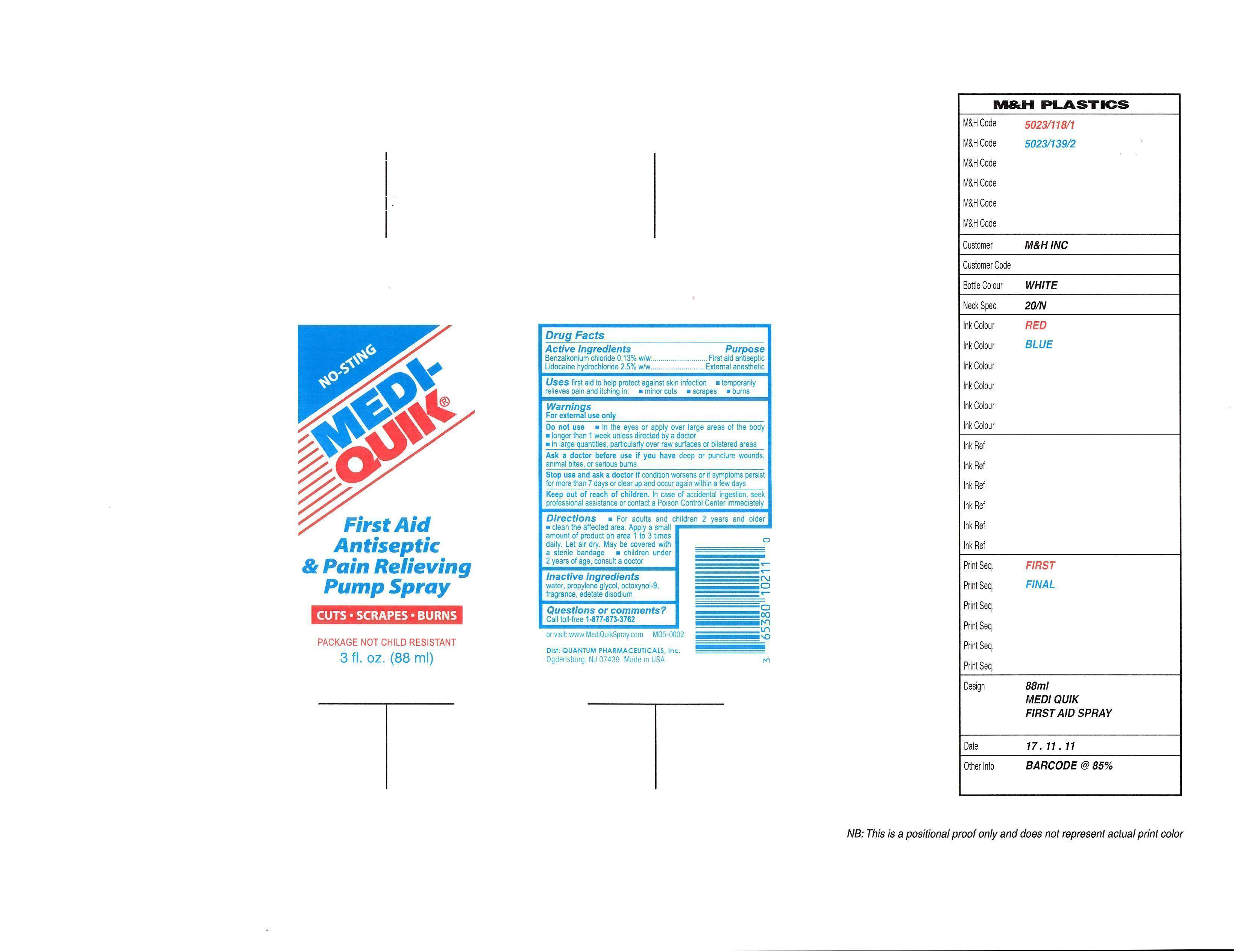 DRUG LABEL: Medi-Quik First Aid Antiseptic
NDC: 69633-111 | Form: SPRAY, METERED
Manufacturer: Quantum Pharmaceuticals Inc.
Category: otc | Type: HUMAN OTC DRUG LABEL
Date: 20150319

ACTIVE INGREDIENTS: BENZALKONIUM CHLORIDE 0.0013 g/1 g; LIDOCAINE HYDROCHLORIDE ANHYDROUS 0.025 g/1 g
INACTIVE INGREDIENTS: WATER; PROPYLENE GLYCOL; octoxynol-9; EDETATE DISODIUM

Drug Facts

Active Ingredients Purpose

Benzalkonium chloride 0.13% w/w..............................................................First aid antiseptic

Lidocaine hydrochloride 2.5% w/w..............................................................External anesthetic

Purpose

Uses: first aid to help protect against skin infection *temporarily relieves pain and itching in: *minor cuts *scrapes *burns

Warnings

FOR EXTERNAL USE ONLY

Stop use and ask a doctor if condition worsens or if symptoms persist for more than 7 days or clear up and occur again within a few days

Indications and Usage

Uses first aid to help protect against skin infection *temporarily relieves pain and itching in: *minor cuts *scrapes *burns

Keep out of reach of children. In case of accidential ingestion, seek professional assistance or contact a Poison Control Center immediately

Dosage and Administration

*For adults and children 2 years and older *Clean the affected area. Apply a small amount of product on area 1 to 3 times daily. let air dry. May be covered with a sterile bandage. *children under 2 years of age, consult a doctor

Inactive Ingredients

water, propylene glycol, octoxynol-9, fragrance, edetate disodium

Do not use *in the eyes or apply over large areas of the body * longer than 1 week unless directed by a doctor * in large quantities, particularly over raw surfaces or blistered areas

Ask a doctor

Stop use and ask a doctor if condition worsens or if symptoms persist for more than 7 days or clear up and occur again within a few days

Directions

*For adults and children 2 years and older *clean the affected area. Apply a small amount of product on area 1 to 3 times daily. Let air dry. May be covered with a sterile bandage. *children under 2 years of age, consult a doctor